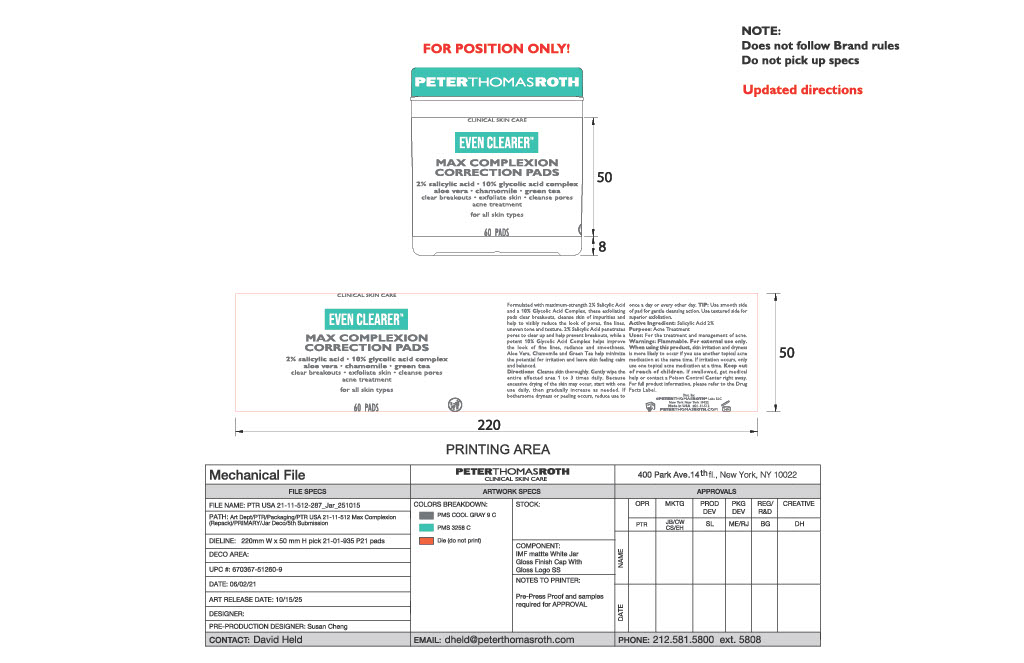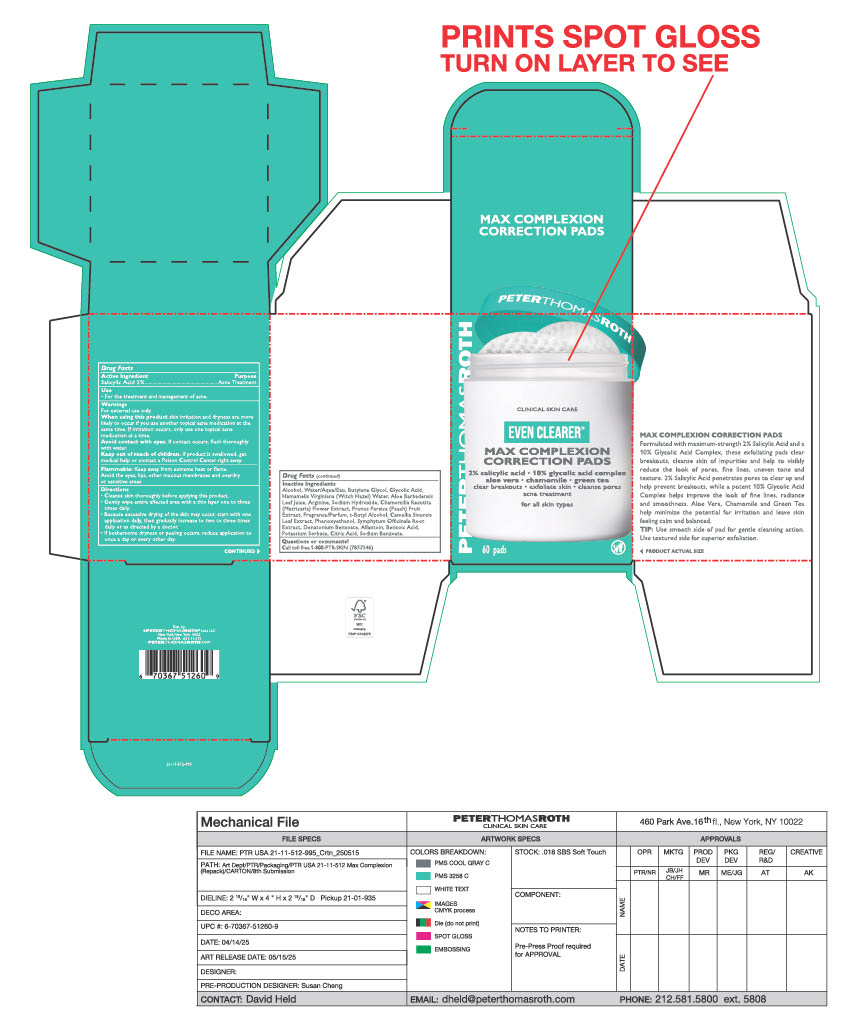 DRUG LABEL: MAX COMPLEXION CORRECTION PADS
NDC: 54031-501 | Form: LIQUID
Manufacturer: PETER THOMAS ROTH LABS LLC
Category: otc | Type: HUMAN OTC DRUG LABEL
Date: 20260115

ACTIVE INGREDIENTS: SALICYLIC ACID 2 g/100 mL
INACTIVE INGREDIENTS: 2-T-BUTYLCYCLOHEXYL ACETATE; BENZYL ACETATE; IONONE; COMFREY ROOT; WATER; PRUNUS PERSICA (PEACH) FRUIT; POTASSIUM SORBATE; PHENOXYETHANOL; LINALOOL; CITRONELLOL; ALOE BARBADENSIS LEAF JUICE; SODIUM HYDROXIDE; CITRIC ACID; CHAMOMILE; BENZOIC ACID; AMYL CINNAMAL; PHENETHYL ALCOHOL; ISOBUTYL METHYL TETRAHYDROPYRANOL; DIMETHYL PHENETHYL BUTYRATE; DENATONIUM BENZOATE; LIMONENE, (+)-; ALLANTOIN; SODIUM BENZOATE; ARGININE; GAMMA-DECALACTONE; ALCOHOL; GLYCOLIC ACID; BUTYLENE GLYCOL; T-BUTYL ALCOHOL; CAMELLIA SINENSIS LEAF; GERANIOL; HAMAMELIS VIRGINIANA TOP WATER; ACETYL HEXAMETHYL TETRALIN; GAMMA-UNDECALACTONE

MAX COMPLEXION CORRECTION PADS (32-50-1)

Active Ingredient

Salicylic Acid 2%

PURPOSE

Acne Treatment

USE

- For the treatement and management of acne .

Warnings

For external use only.

When using this product skin irritation and dryness are more likely to occur if you use another topical acne medication at the same time. If Irritation occurs, only use one topical medication at a time.

Avoid contact with eyes. If contact occurs, flush thoroughly with water

Keep Out of reach of children. If product is swallowed, get medical help or contact a Poison Control Center right away.

OTHER SAFETY INFORMATION

Flammable: Keep away from extreme heat or flame.

Avoid the eyes, lips., other mucous membranes and overdry or sensitive areas.

Directions

- Cleanse skin thoroughly before applying this product.
- Gently wipe entire affected area with a thin layer one to three times a day.
- Because excessive drying of the skin may occur, start with one application daily, then gradually increase to two to three times daily or as directed by a doctor.
- If bothersome dryness or peeling occurs, reduce application to once a day or everyother day.

Inactive Ingredients

Alcohol, Water/Aqua/Eau, Butylne glycol, Glycolic Acid, Hamamelis Virginiana (Witch Hazel) Water, Aloe Barbadensis Leaf Juice, Arginine, Sodium Hydroxide, Chamomilla Recutita (Matricaria) Flower Extract, Prunus Persia (Peach) Fruit Extract, Fragrance/Parfum, t-Butyl Alcohol, Camellia Sinensis Leaf Extract, Phenoxyethanol, Symphytum Officinale Root Extract, Denatonium Benzoate, Allantoin, Benzoic Acid, Potassium Sorbate, Citric Acid, Sodium Benzoate.

Questions or comments

Call toll free 1-800-PTR-SKIN (787-7546)